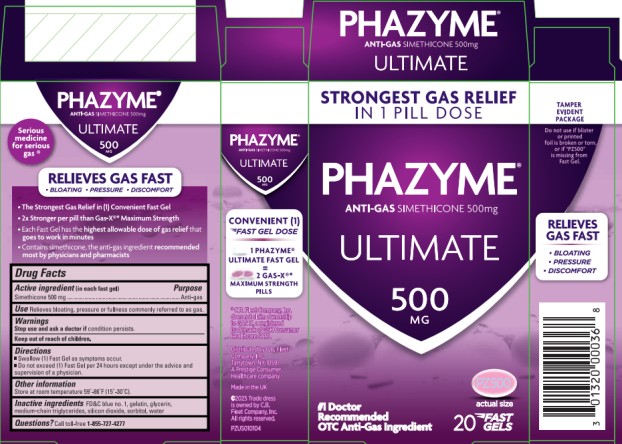 DRUG LABEL: Phazyme Ultimate
NDC: 0132-0222 | Form: CAPSULE, LIQUID FILLED
Manufacturer: C.B. Fleet Company, Inc.
Category: otc | Type: HUMAN OTC DRUG LABEL
Date: 20251023

ACTIVE INGREDIENTS: DIMETHICONE 500 mg/1 1
INACTIVE INGREDIENTS: FD&C BLUE NO. 1; WATER; GELATIN; GLYCERIN; MEDIUM-CHAIN TRIGLYCERIDES; SILICON DIOXIDE; SORBITOL

Phazyme Ultimate 500 mg _0132-0222

Drug Facts

Active Ingredient (in each fast gel)

Simethicone 500mg

Purpose

Anti-gas

Use

- Relieves bloating, pressure, or fullness commonly referred to as gas.

Warnings:

Stop use and ask a doctor if

condition persists.

Directions

- Swallow (1) Fast Gel as symptoms occur
- Do not exceed (1) Fast Gel per 24 hours except under the advice and supervision of a physician

Other information

- Store at room temperature 59°- 86°F (15°-30°C).

Inactive Ingredients

FD&C blue no. 1, gelatin, glycerin, medium-chain triglycerides, silicon dioxide, sorbitol, water

Questions?

Call toll-free 1-855-727-4277

Principal Display Panel

PHAZYME®
ANTI-GAS SIMETHICONE 500mg

ULTIMATE
500 MG